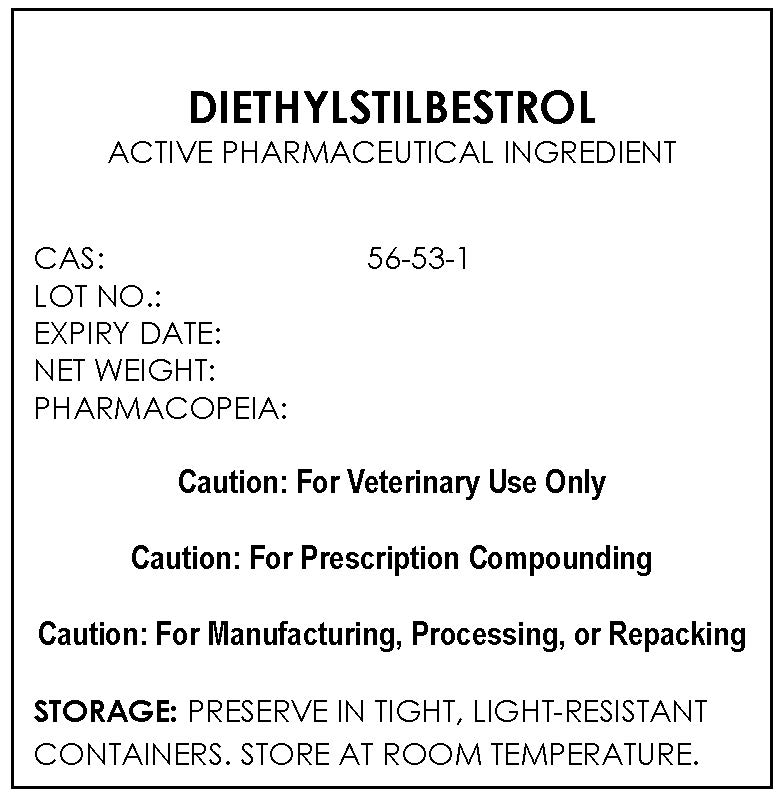 DRUG LABEL: DIETHYLSTILBESTROL
NDC: 43744-094 | Form: POWDER
Manufacturer: CBSCHEM LIMITED
Category: other | Type: BULK INGREDIENT
Date: 20211113

ACTIVE INGREDIENTS: DIETHYLSTILBESTROL 1 g/1 g

DIETHYLSTILBESTROL

PACKAGE LABEL

diethylstilbestrollabelfile.jpg